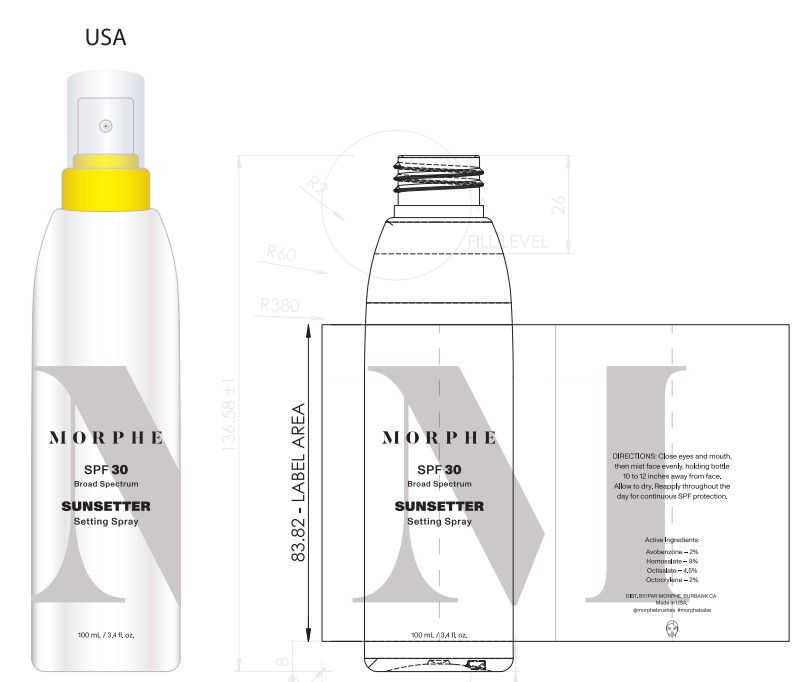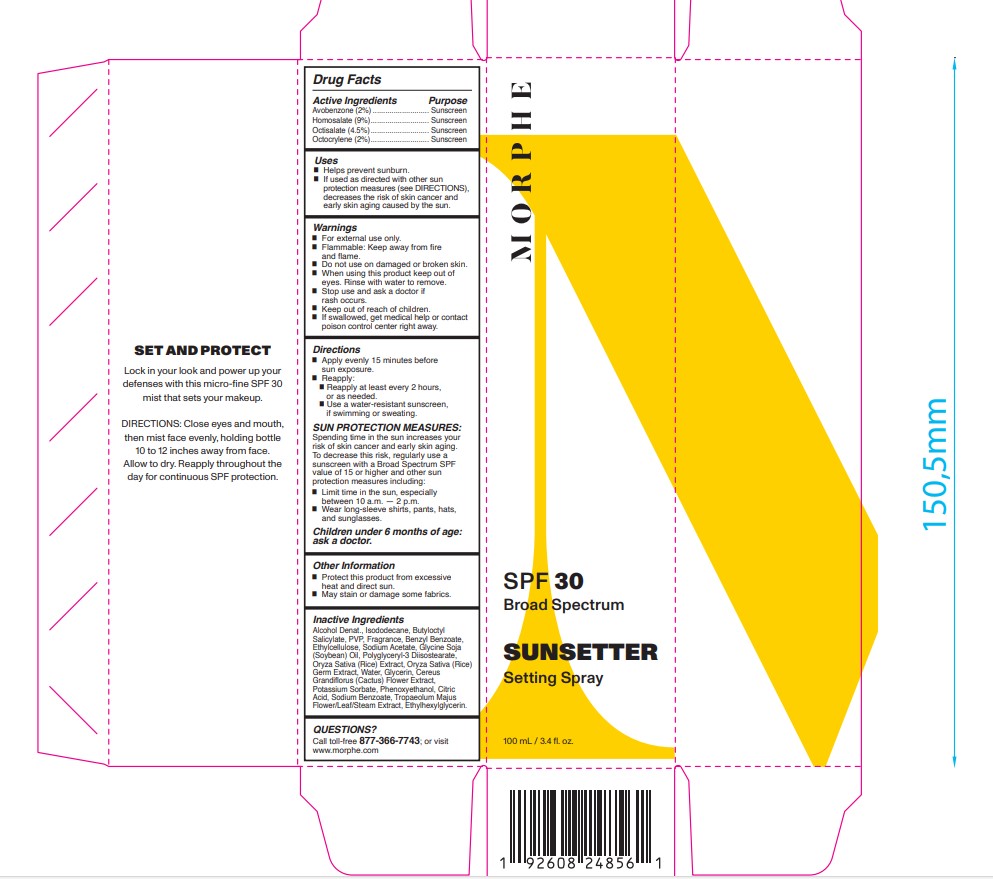 DRUG LABEL: Morphe SPF 30 Broad Spectrum Sunsetter Setting
NDC: 68577-151 | Form: SPRAY
Manufacturer: COSMAX USA, CORPORATION
Category: otc | Type: HUMAN OTC DRUG LABEL
Date: 20241226

ACTIVE INGREDIENTS: AVOBENZONE 2 mg/100 mg; HOMOSALATE 9 mg/100 mg; OCTOCRYLENE 2 mg/100 mg; OCTISALATE 4.5 mg/100 mg
INACTIVE INGREDIENTS: ALCOHOL; ISODODECANE; BUTYLOCTYL SALICYLATE; POVIDONE; FRAGRANCE 13576; BENZYL BENZOATE; ETHYLCELLULOSES; SODIUM ACETATE; SOYBEAN OIL; POLYGLYCERYL-3 DIISOSTEARATE; RICE GERM; WATER; GLYCERIN; SELENICEREUS GRANDIFLORUS FLOWER; POTASSIUM SORBATE; PHENOXYETHANOL; ANHYDROUS CITRIC ACID; SODIUM BENZOATE; TROPAEOLUM MAJUS FLOWERING TOP; ETHYLHEXYLGLYCERIN

Morphe SPF30 Broad Spectrum Sunsetter Setting Spray

Active Ingredients

Avobenzone 2%

Homosalate 9%

Octisalate 4.5%

Octocrylene 2%

Purpose

Sunscreen

USES

- helps prevent sunburn
- if used as directed with other sun protection measures (see Directions), decreases the risk of skin cancer and early skin aging cause by the sun

Warnings

For extenal use only

Flammable

Flammable: Keep away from fire and flame.

Do not useon damaged or broken skin

WHEN USING

When using this productkeep out of eyes. Rinse with water to remove.

Stop use and ask a doctor ifrash occurs

Keep out of reach of children.If swallowed, get medical help or contact a Poison Control Center right away.

DIRECTIONS

- Apply evenly 15 minutes before sun exposure
  - Reapply
  - Reapply at least every 2 hours, or as needed
- Use a water resistant sunscreen if swimming or sweating
  - Sun Protection Measures. Spending time in the sun increases your risk of skin cancer and early skin aging. To decrease this risk, regularly use a sunscreen with a Broad Spectrum SPF value of 15 or higher and other sun protection measures including:

- limit time in the sun, especially from 10 a.m. - 2p.m.

-wear long-sleeved shirts, pants, hats and sunglasses

Children under 6 months of age: Ask a doctor

OTHER INFORMATION

- Protect the product in this container from excessive heat and direct sun
- May stain or damage some fabrics.

INACTIVE INGREDIENT

Inactive ingredients: Alcohol Denat., Isododecane, Butyloctyl Salicylate, PVP, Fragrance, Benzyl Benzoate, Ethylcellulose, Sodium Acetate, Glycine Soja (Soybean) Oil, Polyglyceryl-3 Diisostearate, Oryza Sativa (Rice) Extract, Oryza Sativa (Rice) Germ Extract, Water, Glycerin, Cereus Grandiflorus (Cactus) Flower Extract, Potassium Sorbate, Phenoxyethanol, Citric Acid, Sodium Benzoate, Tropaeolum Majus Flower/Leaf/Steam Extract, Ethylhexylglycerin.

QUESTIONS or COMMENTS

1-8771-877-900-6700 Monday - Friday (9 a.m. - 5 p.m. EST)

Primary Package(Inner)

Outer Package